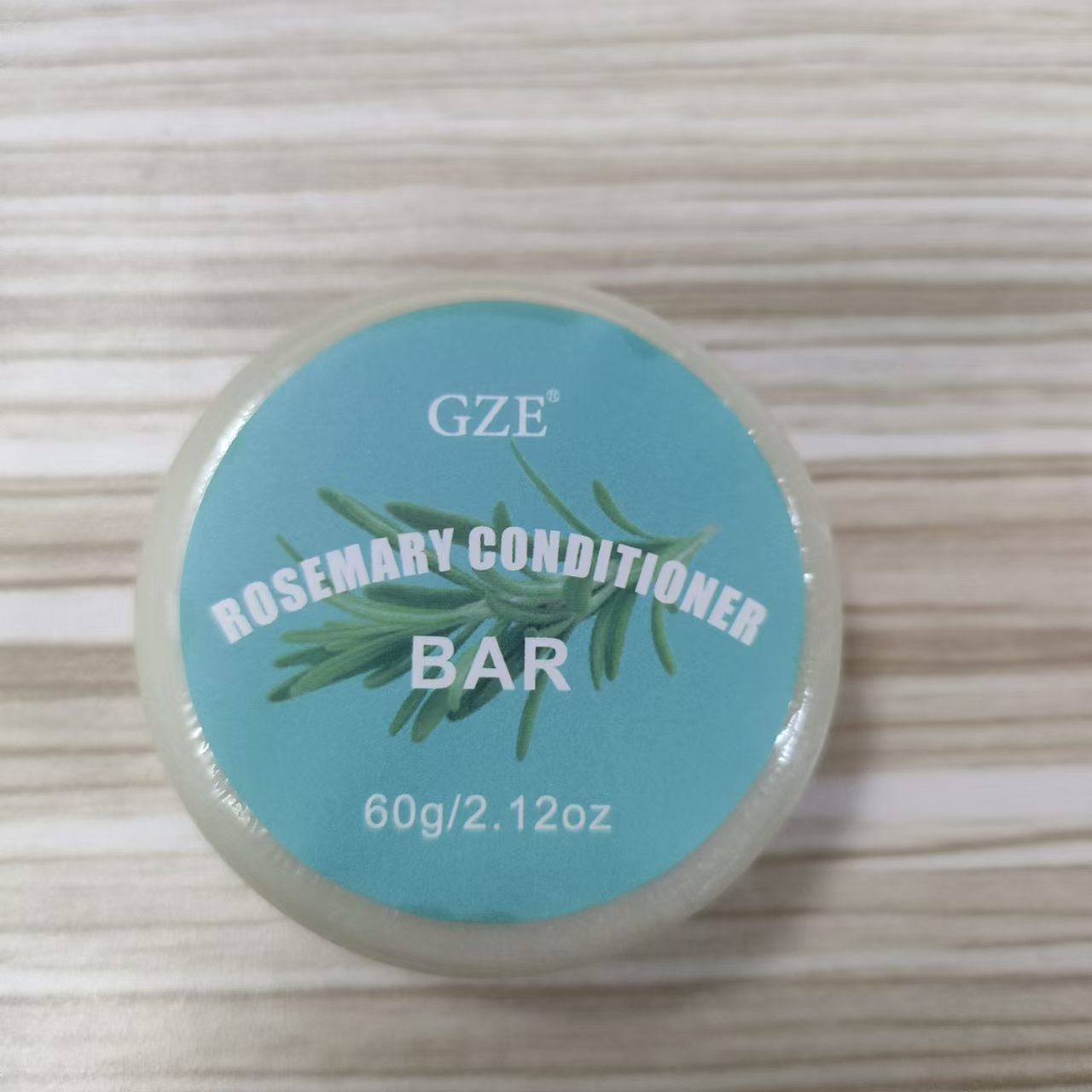 DRUG LABEL: GZE ROSEMARY CONDITIONER BAR
NDC: 74458-256 | Form: SOAP
Manufacturer: Guangzhou Yilong Cosmetics Co., Ltd
Category: otc | Type: HUMAN OTC DRUG LABEL
Date: 20241009

ACTIVE INGREDIENTS: ROSEMARY 46 g/100 g
INACTIVE INGREDIENTS: COCONUT OIL; CASTOR OIL; PANTHENOL; TOCOPHEROL; PARFUMIDINE; COCOA BUTTER

GZE ROSEMARY CONDITIONER BAR

INACTIVE INGREDIENT

Ricinus Communis (Castor) Seed Oil

Cocos Nucifera (Coconut) Oil

Theobroma Cacao (Cocoa) Seed Butter

Panthenol

Tocopherol

Parfum

PURPOSE

Dandruff.

INDICATIONS AND USAGE

After shampooing,while water runs over hair, slide conditioner barover hair, work into the ends then rinse. For deeper conditioning,repeat.

WARNINGS

For external use only.

Stop use and ask a doctor if rash occurs.

Do not use on damaged or broken skin.

When using this product keep out of eyes. Rinse with water to remove.

Keep out of reach of children. If swallowed, get medical help or contact a Poison Control Center right away.

DOSAGE AND ADMINISTRATION

After shampooing,while water runs over hair, slide conditioner bar over hair, work into the ends then rinse. For deeper conditioning,repeat.